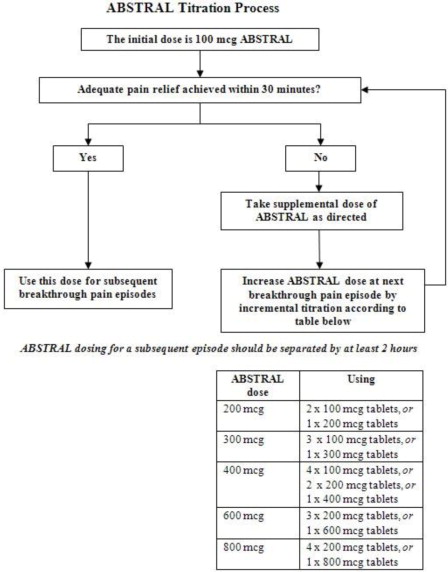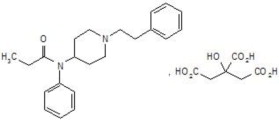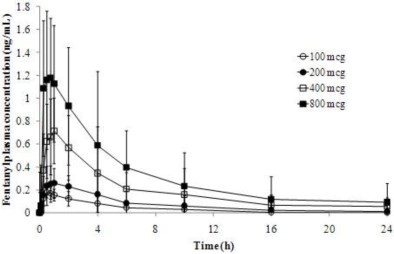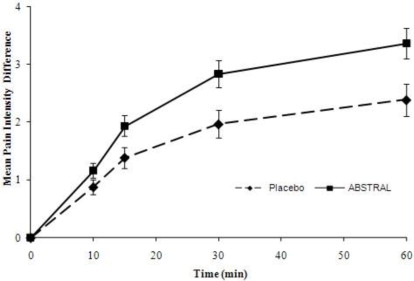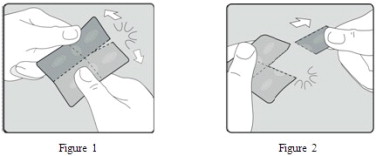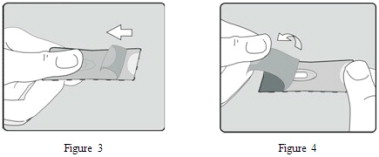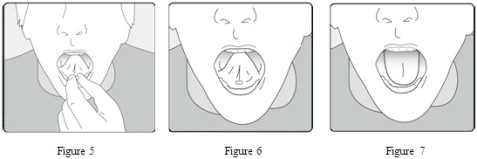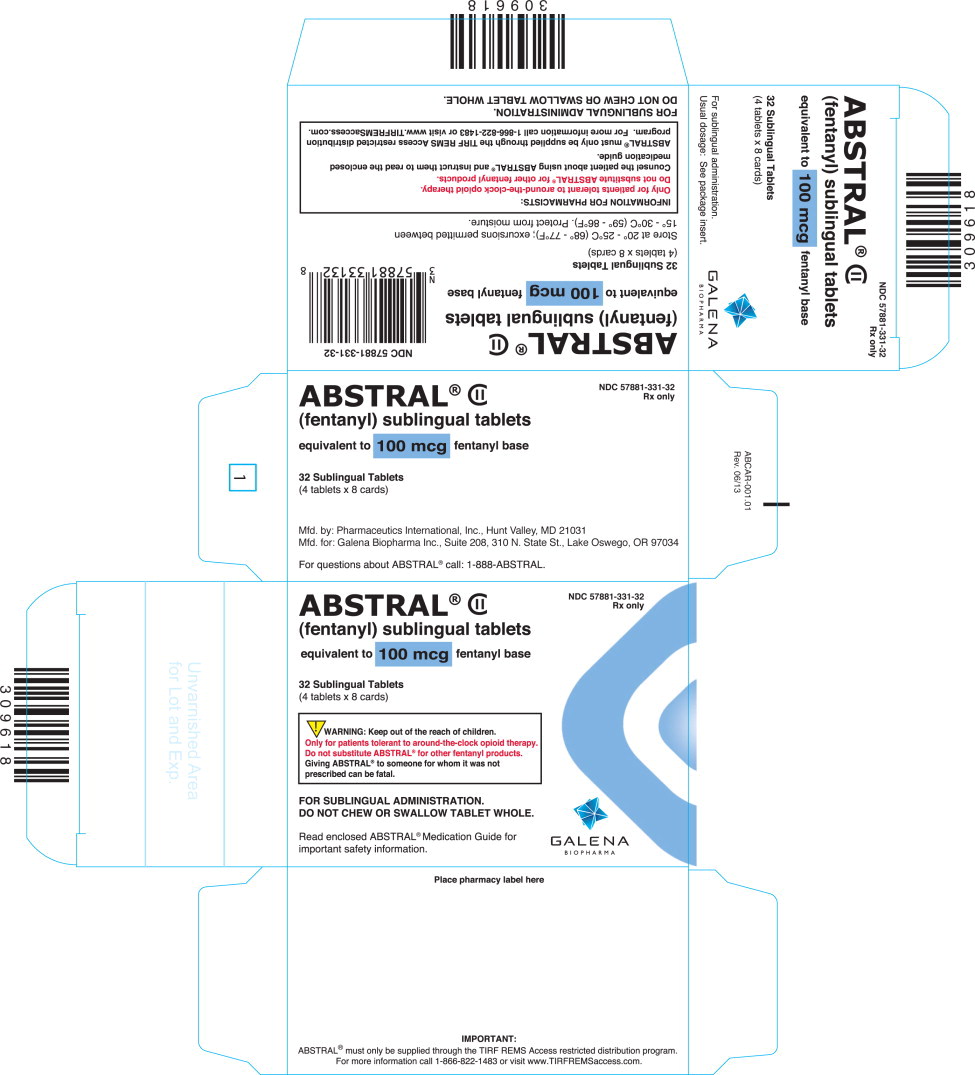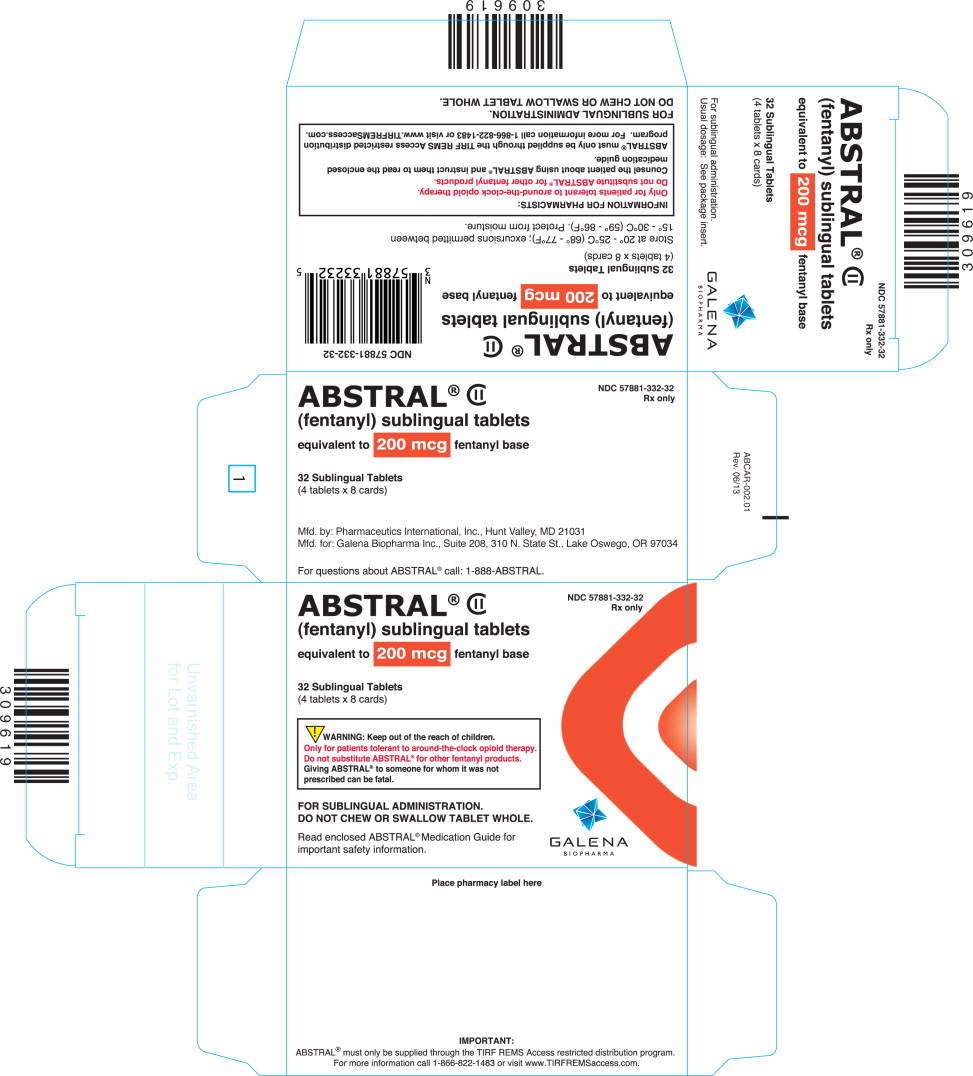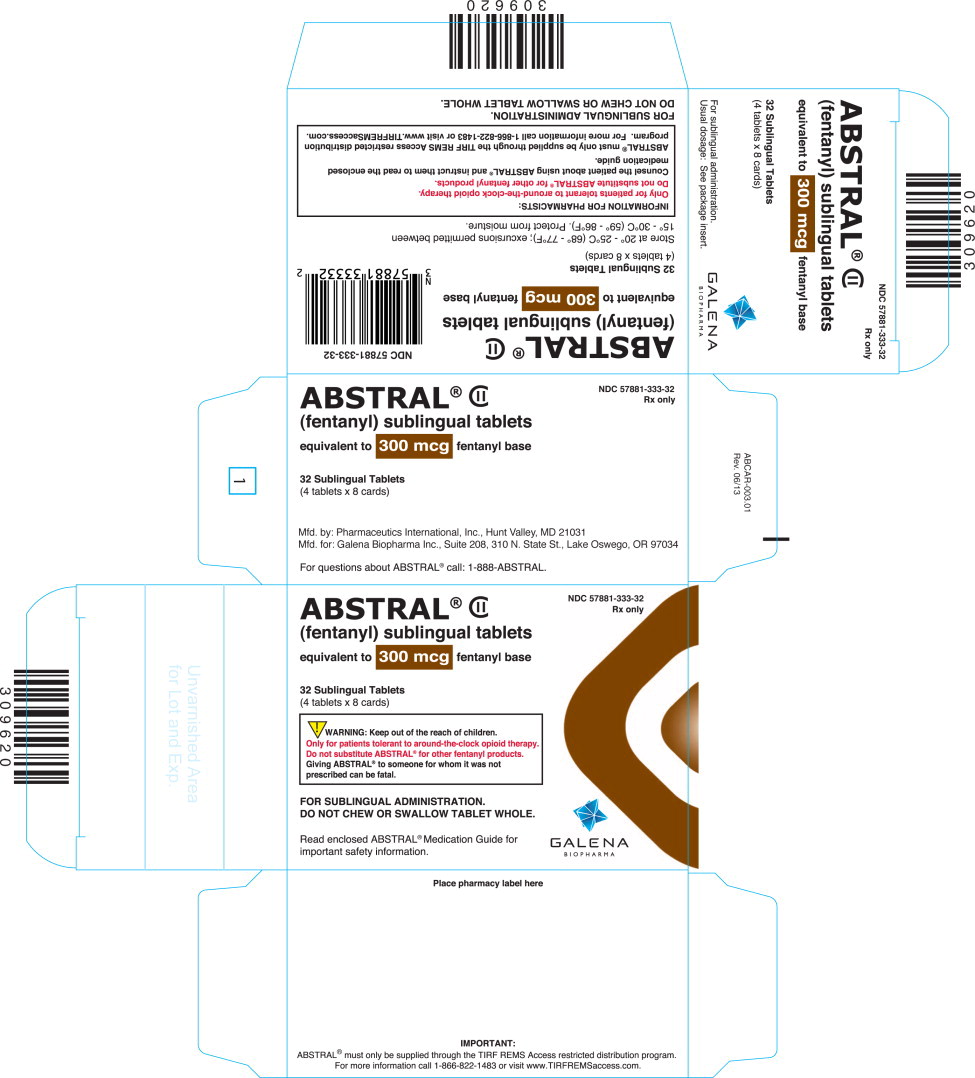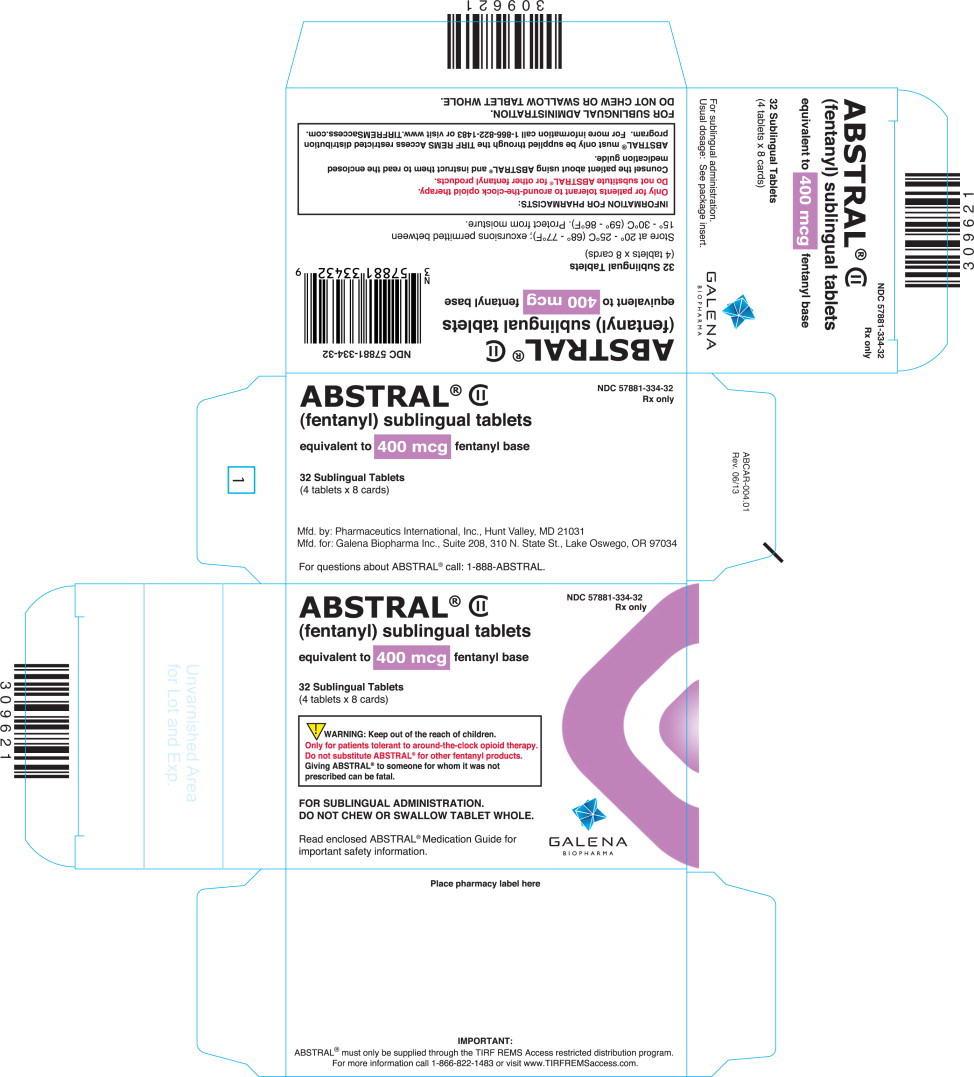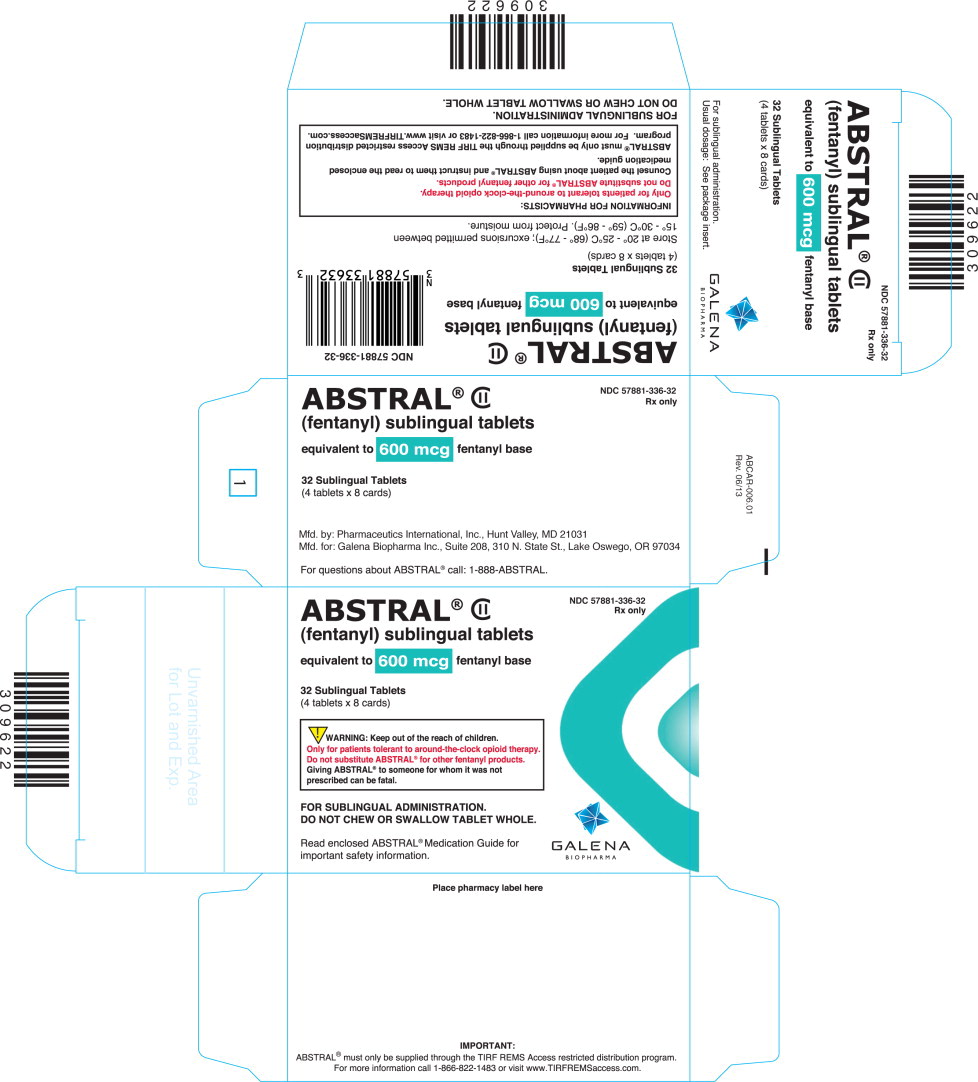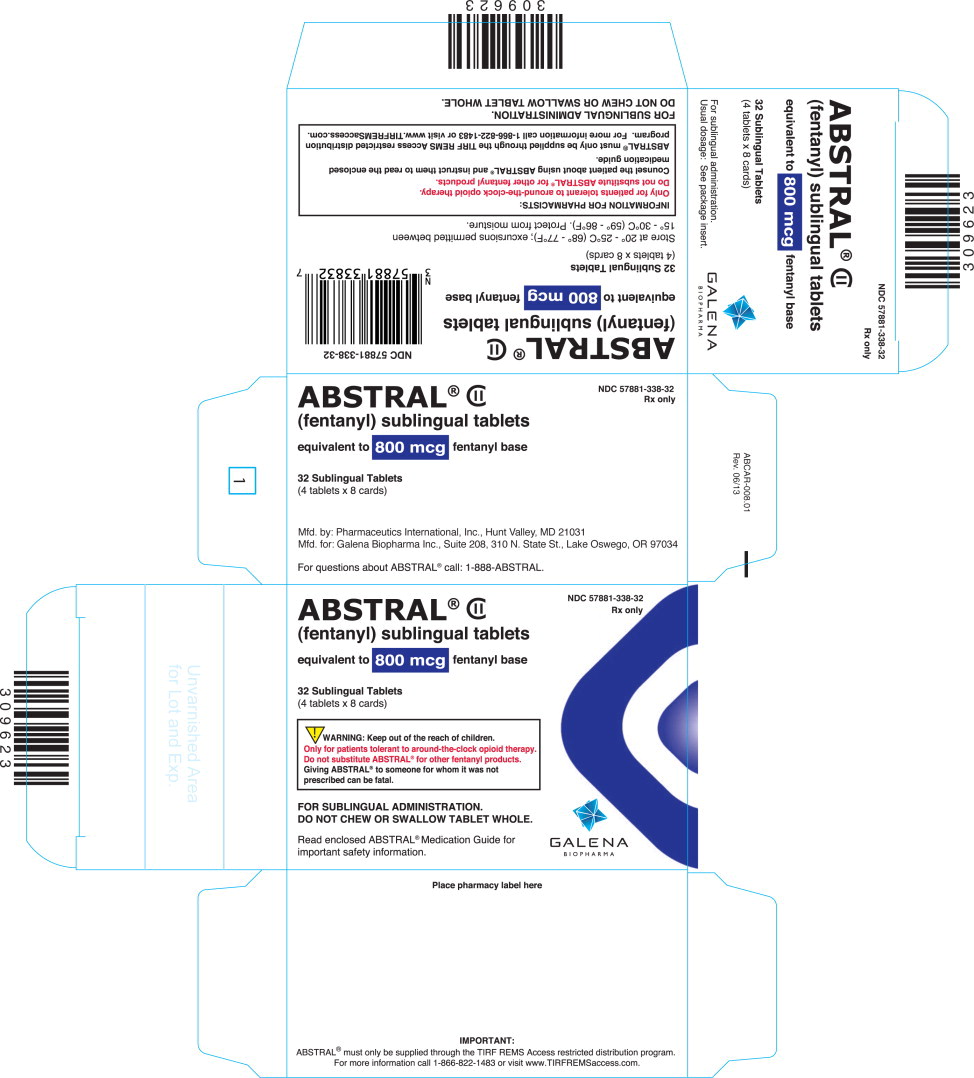 DRUG LABEL: Abstral
NDC: 57881-331 | Form: TABLET
Manufacturer: Galena Biopharma, Inc.
Category: prescription | Type: HUMAN PRESCRIPTION DRUG LABEL
Date: 20141130
DEA Schedule: CII

ACTIVE INGREDIENTS: fentanyl citrate 100 ug/1 1
INACTIVE INGREDIENTS: croscarmellose sodium; magnesium stearate; mannitol; cellulose, microcrystalline

HIGHLIGHTS OF PRESCRIBING INFORMATION

These highlights do not include all the information needed to use ABSTRAL safely and effectively. See full prescribing information for ABSTRAL.
ABSTRAL® (fentanyl) sublingual tablets CII
Initial U.S. Approval: 1968

RECENT MAJOR CHANGES

Dosage and Administration, Conversion from Actiq (2.2) 11/2014

WARNING: RISK OF RESPIRATORY DEPRESSION, MEDICATION ERRORS, ABUSE POTENTIAL

WARNING: RISK OF RESPIRATORY DEPRESSION,
MEDICATION ERRORS, ABUSE POTENTIAL

See full prescribing information for complete boxed warning.

- Due to the risk of fatal respiratory depression, ABSTRAL is contraindicated in opioid non-tolerant patients (1) and in management of acute or postoperative pain, including headache/migraines. (4)
- Keep out of reach of children. (5.3)
- Use with CYP3A4 inhibitors may cause fatal respiratory depression.
- (7)
- When prescribing, do not convert patients on a mcg per mcg basis from any other oral transmucosal fentanyl product to ABSTRAL. (2.1, 5.2)
- When dispensing, do not substitute with any other fentanyl products. (5.2)
- Contains fentanyl, a Schedule II controlled substance with abuse liability similar to other opioid analgesics. (9.1)
- ABSTRAL is available only through a restricted program called the TIRF REMS Access program. Outpatients, healthcare professionals who prescribe to outpatients, pharmacies, and distributors are required to enroll in the program. (5.10)

1 INDICATIONS AND USAGE

ABSTRAL is an opioid agonist indicated for the management of breakthrough pain in cancer patients 18 years of age and older who are already receiving and who are tolerant to opioid therapy for their underlying persistent cancer pain. (1) Limitations of Use:

ABSTRAL may be dispensed only to patients enrolled in the TIRF REMS Access program.

2 DOSAGE AND ADMINISTRATION

- Patients must require and use around-the-clock opioids when taking ABSTRAL (1)
- Initial dose of ABSTRAL: 100 mcg. (2.1)
- Individually titrate to a tolerable dose that provides adequate analgesia. (2.1)
- No more than two doses can be taken per breakthrough pain episode. (2.1)
- Wait at least 2 hours before treating another episode of breakthrough pain
- with ABSTRAL. (2.1)
- Limit consumption to treat four or fewer breakthrough pain episodes per day once a successful dose is found. (2.4)
- Administer on the floor of the mouth directly under the tongue and allow to completely dissolve. (2.5)

3 DOSAGE FORMS AND STRENGTHS

- Sublingual tablet in 100 mcg, 200 mcg, 300 mcg, 400 mcg, 600 mcg and 800 mcg strengths. (3)

4 CONTRAINDICATIONS

- Opioid non-tolerant patients. (4)
- Management of acute or postoperative pain including headache/migraines dental pain. (4)
- Intolerance or hypersensitivity to fentanyl or components of ABSTRAL. (4)

5 WARNINGS AND PRECAUTIONS

- Clinically significant respiratory and CNS depression can occur. Monitor patients accordingly. (5.1, 5.4)
- Do not convert patients on a mcg per mcg basis from another fentanyl product to ABSTRAL. (5.2)
- ABSTRAL contains fentanyl in a dose that can be fatal to a child. Ensure proper storage and disposal. (5.3, 16.3)
- Use with other CNS depressants and potent cytochrome P450 3A4 inhibitors may increase depressant effects including hypoventilation, hypotension, and profound sedation. Consider dosage adjustments if warranted. (5.4, 7)
- Titrate ABSTRAL cautiously in patients with chronic obstructive pulmonary disease or pre-existing medical conditions predisposing them to hypoventilation, and in patients susceptible to intracranial effects of CO2 retention. (5.6, 5.7)

6 ADVERSE REACTIONS

- Most common (total frequency ≥ 3%): nausea, somnolence, headache, and constipation. (6.1)

To report SUSPECTED ADVERSE REACTIONS, contact Galena Biopharma, Inc. at 1-888-227-8725 or FDA at 1-800-FDA-1088 or www.fda.gov/ medwatch.

7 DRUG INTERACTIONS

- See Boxed Warning and Warnings and Precautions (5)

8 USE IN SPECIFIC POPULATIONS

- Administer ABSTRAL with caution to patients with renal or hepatic dysfunction. (8.6)

FULL PRESCRIBING INFORMATION

WARNING: RISK OF RESPIRATORY DEPRESSION, MEDICATION ERRORS, ABUSE POTENTIAL

RESPIRATORY DEPRESSION

Fatal respiratory depression has occurred in patients treated with immediate-release transmucosal fentanyl, including following use in opioid non-tolerant patients and improper dosing. The substitution of ABSTRAL for any other fentanyl product may result in fatal overdose.

Due to the risk of respiratory depression, ABSTRAL is contraindicated in the management of acute or postoperative pain including headache/migraine and in opioid non-tolerant patients. [see Contraindications (4)]

ABSTRAL must be kept out of reach of children. [see Patient Counseling Information (17.1) and How Supplied/Storage and Handling (16.1)]

The concomitant use of ABSTRAL with CYP3A4 inhibitors may result in an increase in fentanyl plasma concentrations, and may cause potentially fatal respiratory depression. [see Drug Interactions (7)]

MEDICATION ERRORS

Substantial differences exist in the pharmacokinetic profile of ABSTRAL compared to other fentanyl products that result in clinically important differences in the extent of absorption of fentanyl that could result in fatal overdose.

- When prescribing, do not convert patients on a mcg per mcg basis from any other fentanyl products to ABSTRAL. (2.1)
- When dispensing, do not substitute an ABSTRAL prescription for other fentanyl products.

ABUSE POTENTIAL

ABSTRAL contains fentanyl, an opioid agonist and a Schedule II controlled substance, with an abuse liability similar to other opioid analgesics. ABSTRAL can be abused in a manner similar to other opioid agonists, legal or illicit. This should be considered when prescribing or dispensing ABSTRAL in situations where the physician or pharmacist is concerned about an increased risk of misuse, abuse or diversion.

Because of the risk for misuse, abuse, addiction, and overdose, ABSTRAL is available only through a restricted program, required by the Food and Drug Administration, called a Risk Evaluation and Mitigation Strategy (REMS). Under the TIRF (Transmucosal Immediate Release Fentanyl) REMS Access program, outpatients, healthcare professionals who prescribe to outpatients, pharmacies, and distributors must enroll in the program [see Warnings and Precautions (5.10)]. Further information is available at www.TIRFREMSAccess.com or by calling1-866-822-1483.

1 INDICATIONS AND USAGE

ABSTRAL (fentanyl) sublingual tablets are indicated for the management of breakthrough pain in cancer patients 18 years of age and older who are already receiving and who are tolerant to opioid therapy for their underlying persistent cancer pain. Patients considered opioid tolerant are those who are taking around-theclock medicine consisting of at least 60 mg of oral morphine daily, or at least 25 mcg of transdermal fentanyl/hour, or at least 30 mg of oral oxycodone daily, or at least 8 mg of oral hydromorphone daily or at least 25 mg oral oxymorphone daily, or an equianalgesic dose of another opioid medication daily for a week or longer. Patients must remain on around-the-clock opioids when taking ABSTRAL.

ABSTRAL is contraindicated for patients who are not already tolerant to opioids because life-threatening respiratory depression and death could result at any dose in patients not on a chronic regimen of opioids. For this reason, ABSTRAL is contraindicated in the management of acute or postoperative pain, including headache/migraine, dental pain, or use in the emergency room.

ABSTRAL is intended to be prescribed only by healthcare professionals who are knowledgeable of, and skilled in, the use of Schedule II opioids to treat cancer pain.

Limitations of Use:

As a part of the TIRF REMS Access program, ABSTRAL may be dispensed only to outpatients enrolled in the program [see Warnings and Precautions (5.10)]. For inpatient administration of ABSTRAL (e.g., hospitals, hospices, and long-term care facilities that prescribe for inpatient use), patient and prescriber enrollment is not required.

2 DOSAGE AND ADMINISTRATION

Healthcare professionals who prescribe ABSTRAL on an outpatient basis must enroll in the TIRF REMS

Access program and comply with the requirements of the REMS to ensure safe use of ABSTRAL [See Warnings and Precautions (5.10)].

As with all opioids, the safety of patients using such products is dependent on health care professionals prescribing them in strict conformity with their approved labeling with respect to patient selection, dosing, and proper conditions for use.

2.1 Dose Titration

The objective of dose titration is to identify an effective and tolerable maintenance dose for ongoing management of breakthrough cancer pain episodes. The effective and tolerable dose of ABSTRAL will be determined by dose titration in individual patients.

Carefully supervise patients until a dose that provides adequate analgesia with tolerable side effects is reached for breakthrough pain control.

Starting Dose: Individually titrate ABSTRAL to a dose that provides adequate analgesia with tolerable side effects. Begin titration of all patients with an initial dose of ABSTRAL of 100 mcg. Due to differences in the pharmacokinetic properties and individual variability, even patients switching from other fentanyl containing products to ABSTRAL must start with the 100 mcg dose. However, for patients converting from Actiq, see Table 1: Initial Dosing Recommendations for Patients on ACTIQ. ABSTRAL is not equivalent on a mcg per mcg basis with all other fentanyl products, therefore, do not switch patients on a mcg per mcg basis from any other fentanyl product. ABSTRAL is NOT a generic version of any other fentanyl product.

Start all patients with a single 100 mcg tablet.

- If adequate analgesia is obtained within 30 minutes of administration of the 100 mcg tablet, continue to treat subsequent episodes of breakthrough pain with this dose.
- If adequate analgesia is not obtained after ABSTRAL, the patient may use a second ABSTRAL dose (after 30 minutes) as directed by their health care provider. No more than two doses of ABSTRAL may be used to treat an episode of breakthrough pain.
- Patients must wait at least 2 hours before treating another episode of breakthrough pain with ABSTRAL.

Titration Steps: If adequate analgesia was not obtained with the first 100 mcg dose, continue dose escalation in a stepwise manner over consecutive breakthrough episodes until adequate analgesia with tolerable side effects is achieved. Increase the dose by 100 mcg multiples up to 400 mcg as needed. If adequate analgesia is not obtained with a 400 mcg dose, the next titration step is 600 mcg. If adequate analgesia is not obtained with a 600 mcg dose, the next titration step is 800 mcg. During titration, patients can be instructed to use multiples of 100 mcg tablets and/or 200 mcg tablets for any single dose. Instruct patients not to use more than 4 tablets at one time. If adequate analgesia is not obtained 30 minutes after the use of ABSTRAL, the patient may repeat the same dose of ABSTRAL. No more than two doses of ABSTRAL may be used to treat an episode of breakthrough pain. Rescue medication as directed by the health care provider can be used if adequate analgesia is not achieved after use of ABSTRAL.

The efficacy and safety of doses higher than 800 mcg have not been evaluated in clinical studies in patients.

In order to minimize the risk of ABSTRAL-related adverse reactions and to identify the appropriate dose, it is imperative that patients be supervised closely by health professionals during the titration process.

2.2 Conversion from Actiq

The initial dose of Abstral is always 100 mcg with the only exception being patients already using Actiq.

1. For patients being converted from Actiq, prescribers must use the Initial Dosing Recommendations for Patients on Actiq. See Table 1 for initial dosing recommendations. Patients must be instructed to stop the use of Actiq and dispose of any remaining units.
  Table 1: Initial Dosing Recommendations for Patients on ACTIQ
  Current ACTIQ Dose (mcg) Initial Abstral Dose (mcg)
  200 | 100 mcg
  400 | 200 mcg
  600 | 200 mcg
  800 | 200 mcg
  1200 | 200 mcg
  1600 | 400 mcg
2. For patients converting from Actiq doses of 200 mcg and 400 mcg, initiate titration with 100 mcg and 200 mcg of Abstral, respectively and proceed using multiples of this strength.
3. For patients converting from Actiq doses of 600 and 800 mcg, initiate titration with 200 mcg and 200 mcg Abstral, respectively and proceed using multiples of this strength.
4. For patients converting from Actiq doses of 1200 and 1600 mcg, initiate titration with 200 mcg and 400 mcg Abstral, respectively and proceed using multiples of this strength.

2.3 Maintenance Therapy

Once an appropriate dose for pain management has been established, instruct patients to use only one ABSTRAL tablet of the appropriate strength per dose. Maintain patients on this dose.

If adequate analgesia is not obtained after use of ABSTRAL, the patient may use a second ABSTRAL dose (after 30 minutes) as directed by their health care provider. No more than two doses of ABSTRAL may be used to treat an episode of breakthrough pain.

Patients must wait at least 2 hours before treating another episode of breakthrough pain with ABSTRAL.

2.4 Dose Re-adjustment

If the response (analgesia or adverse reactions) to the titrated ABSTRAL dose markedly changes, an adjustment of dose may be necessary to ensure that an appropriate dose is maintained.

If more than four episodes of breakthrough pain are experienced per day, re-evaluate the dose of the longacting opioid used for persistent underlying cancer pain. If the long-acting opioid or dose of long-acting opioid is changed, re-evaluate and re-titrate the ABSTRAL dose as necessary to ensure the patient is on an appropriate dose.

Limit the use of ABSTRAL to treat four or fewer episodes of breakthrough pain per day.

It is imperative that any dose re-titration is monitored carefully by a healthcare professional.

2.5 Administration of ABSTRAL

Place ABSTRAL tablets on the floor of the mouth directly under the tongue immediately after removal from the blister unit. Do not chew, suck, or swallow ABSTRAL tablets. Allow ABSTRAL tablets to completely dissolve in the sublingual cavity. Advise patients not to eat or drink anything until the tablet is completely dissolved.

In patients who have a dry mouth, water may be used to moisten the buccal mucosa before taking ABSTRAL.

2.6 Discontinuation of Therapy

For patients no longer requiring opioid therapy, consider discontinuing ABSTRAL along with a gradual downward titration of other opioids to minimize possible withdrawal effects.

In patients who continue to take their chronic opioid therapy for persistent pain but no longer require treatment for breakthrough pain, ABSTRAL therapy can usually be discontinued immediately.

3 DOSAGE FORMS AND STRENGTHS

ABSTRAL is formulated as a sublingual tablet and is available in six strengths, distinguishable by the shape of the tablet and by de- bossing on the tablet surface. All tablets are white:

100 microgram tablet is a round tablet marked with the number "1"

200 microgram tablet is an oval-shaped tablet marked with the number "2"

300 microgram tablet is a triangle-shaped tablet marked with the number "3"

400 microgram tablet is a diamond-shaped tablet marked with the number "4"

600 microgram tablet is a "D"-shaped tablet marked with the number "6"

800 microgram tablet is a capsule-shaped tablet marked with the number "8"

[see How Supplied/Storage and Handling (16.4)].

4 CONTRAINDICATIONS

ABSTRAL is contraindicated in the management of pain in opioid non-tolerant patients, because lifethreatening hypoventilation could occur at any dose in patients not already taking around-the-clock opioid therapy. Patients considered opioid tolerant are those who are taking at least 60 mg oral morphine/day, or at least 25 mcg transdermal fentanyl/hour, 30 mg oral oxycodone/day, 8 mg oral hydromorphone/day, 25 mg oral oxymorphone/day, or an equianalgesic dose of another opioid for a week or longer.

ABSTRAL is contraindicated in the management of acute or postoperative pain, including headache/migraine, dental pain, or use in the emergency room.

ABSTRAL is contraindicated in patients with known intolerance or hypersensitivity to any of its components or the drug fentanyl. Anaphylaxis and hypersensitivity have been reported in association with the use of other oral transmucosal fentanyl products.

5 WARNINGS AND PRECAUTIONS

See Boxed Warning- WARNINGS: IMPORTANCE OF PROPER PATIENT SELECTION and POTENTIAL FOR ABUSE

5.1 Hypoventilation (Respiratory Depression)

Serious or fatal respiratory depression can occur even at recommended doses in patients using ABSTRAL. Respiratory depression is more likely to occur in patients with underlying respiratory disorders and elderly or debilitated patients, usually following large initial doses, including ABSTRAL, in opioid non-tolerant patients, or when opioids are given in conjunction with other drugs that depress respiration.

Respiratory depression from opioids is manifested by a reduced urge to breathe and a decreased rate of respiration, often associated with the "sighing" pattern of breathing (deep breaths separated by abnormally long pauses). Carbon dioxide retention from opioid- induced respiratory depression can exacerbate the sedating effects of opioids. This makes overdoses involving drugs with sedative properties and opioids especially dangerous.

5.2 ABSTRAL and Other Fentanyl Products

ABSTRAL is NOT equivalent to all other fentanyl products used to treat breakthrough pain on a mcg per mcg basis. There are differences in the pharmacokinetics of ABSTRAL relative to other fentanyl products which could potentially result in clinically important differences in the amount of fentanyl absorbed and could result in a fatal overdose.

When prescribing ABSTRAL to a patient, DO NOT convert on a mcg to mcg basis from other fentanyl products. Directions for safely converting patients to ABSTRAL from other fentanyl products are not currently available except for Actiq [see Conversion from Actiq (2.2) ]. This includes oral, transdermal, or parenteral formulations of fentanyl. Therefore, for opioid-tolerant patients starting treatment for breakthrough pain, the initial dose of ABSTRAL is 100 mcg. Individually titrate each patient's dose to provide adequate analgesia while minimizing side effects. [See Dosage and Administration (2.1)]

When dispensing ABSTRAL to a patient, DO NOT substitute it for any other fentanyl product prescription.

5.3 Patient/Caregiver Instructions

Patients and their caregivers must be instructed that ABSTRAL contains a medicine in an amount which can be fatal to a child. Even though ABSTRAL is provided in child-resistant packaging, patients and their caregivers must be instructed to keep tablets out of the reach of children. [see How Supplied/Storage and Handling (16.1, 16.2), and Patient Counseling Information (17.1, 17.2)].

Taking ABSTRAL could be fatal in individuals for whom it is not prescribed and for those who are not opioid-tolerant.

Physicians and dispensing pharmacists must specifically question patients or caregivers about the presence of children in the home (on a full time or visiting basis) and counsel them regarding the dangers to children from inadvertent exposure.

5.4 Additive CNS Depressant Effects

The concomitant use of ABSTRAL with other CNS depressants, including other opioids, sedatives or hypnotics, general anesthetics, phenothiazines, tranquilizers, skeletal muscle relaxants, sedating antihistamines, and alcoholic beverages may produce increased depressant effects (e.g., hypoventilation, hypotension, and profound sedation). Concomitant use with potent inhibitors of cytochrome P450 3A4 isoform (e.g., erythromycin, ketoconazole, and certain protease inhibitors) may increase fentanyl levels, resulting in increased depressant effects [see Drug Interactions (7)].

Patients on concomitant CNS depressants must be monitored for a change in opioid effects and the dose of ABSTRAL adjusted, if warranted.

5.5 Effects on Ability to Drive and Use Machines

Opioid analgesics impair the mental and/or physical ability required for the performance of potentially dangerous tasks (e.g., driving a car or operating machinery). Warn patients taking ABSTRAL of these dangers and counsel them accordingly.

5.6 Chronic Pulmonary Disease

Because potent opioids can cause hypoventilation, titrate ABSTRAL with caution in patients with chronic obstructive pulmonary disease or pre-existing medical conditions predisposing them to hypoventilation. In such patients, even normal therapeutic doses of ABSTRAL may further decrease respiratory drive to the point of respiratory failure.

5.7 Head Injuries and Increased Intracranial Pressure

Administer ABSTRAL with extreme caution in patients who may be particularly susceptible to the intracranial effects of CO2 retention such as those with evidence of increased intracranial pressure or impaired consciousness. Opioids may obscure the clinical course of a patient with a head injury; use only if clinically warranted.

5.8 Cardiac Disease

Intravenous administration of fentanyl may produce bradycardia. Therefore, use ABSTRAL with caution in patients with bradyarrhythmias.

5.9 MAO Inhibitors

ABSTRAL is not recommended for use in patients who have received MAO inhibitors within the past 14 days.

Severe and unpredictable potentiation by MAO inhibitors has been reported with opioid analgesics.

5.10 Transmucosal immediate Release Fentanyl (TIRF) Risk Evaluation and Mitigation Strategy (REMS) Access Program

Because of the risk for misuse, abuse, addiction, and overdose [see Drug Abuse and Dependence (9)], ABSTRAL is available only through a restricted program called the TIRF REMS Access program. Under the TIRF REMS Access program, outpatients, healthcare professionals who prescribe to outpatients, pharmacies, and distributors must enroll in the program. For inpatient administration (e.g., hospitals, hospices, and longterm care facilities that prescribe for inpatient use) of ABSTRAL, patient and prescriber enrollment is not required.

Required components of the TIRF REMS Access program are:

- Healthcare professionals who prescribe ABSTRAL must review the prescriber educational materials for the TIRF REMS Access program, enroll in the program, and comply with the REMS requirements.
- To receive ABSTRAL, outpatients must understand the risks and benefits and sign a PatientPrescriber Agreement.
- Pharmacies that dispense ABSTRAL must enroll in the program and agree to comply with the REMS requirements.
- Wholesalers and distributors that distribute ABSTRAL must enroll in the program and distribute only to authorized pharmacies.

Further information, including a list of qualified pharmacies/distributors, is available at www.TIRFREMSAccess.com or by calling 1-866-822-1483.

6 ADVERSE REACTIONS

6.1 Clinical Studies Experience

Because clinical trials are conducted under widely varying conditions, adverse event rates observed in the clinical trials of a drug cannot be directly compared to rates in the clinical trials of another drug and may not reflect the rates observed in practice.

The safety of ABSTRAL has been evaluated in 311 opioid-tolerant cancer patients with breakthrough pain. Two hundred and seventy (270) of these patients were treated in multiple-dose studies. The duration of therapy for patients in multiple-dose studies ranged from 1-405 days with an average duration of 131 days and with 44 patients treated for at least 12 months.

The most commonly observed adverse reactions with ABSTRAL include typical opioid adverse reactions, such as nausea, constipation, somnolence and headache. Expect opioid side effects and manage them accordingly.

The clinical trials of ABSTRAL were designed to evaluate safety and efficacy in treating patients with cancer and breakthrough pain; all patients were taking concomitant opioids, such as sustained-release morphine, sustained-release oxycodone or transdermal fentanyl, for their persistent pain.

The adverse reaction data presented in Table 2 reflect the actual percentage of patients experiencing reactions among patients who received ABSTRAL for breakthrough pain along with concomitant opioid use for persistent pain. There has been no attempt to correct for concomitant use of other opioids, duration of ABSTRAL therapy or cancer-related symptoms.

Table 2 lists adverse reactions with an overall frequency of 5% or greater within the total population that occurred during titration by maximum dose received. The ability to assign ABSTRAL a dose-response relationship to these adverse reactions is limited by the titration schemes used in these studies.

Table2: Adverse Reactions Which Occurred During Titration at a Frequency of ≥ 5%
System Organ Class Preferred term N (%) | 100 mcg (n=22) | 200 mcg (n=23) | 300 mcg (n=55) | 400 mcg (n=38) | 600 mcg (n=52) | 800 mcg (n=80) | Total (n=270)
Gastrointestinal disorders
Nausea | 1 (4.5) | 4 (17.4) | 5 (9.1) | 1 (2.6) | 2 (3.8) | 2 (2.5) | 15 (5.6)
Nervous system disorders
Somnolence | 0 | 2 (8.7) | 4 (7.3) | 2 (5.3) | 2 (3.8) | 2 (2.5) | 12 (4.4)
Dizziness | 0 | 0 | 3 (5.5) | 2 (5.3) | 0 | 1 (1.3) | 6 (2.2)
Headache | 0 | 0 | 0 | 1 (2.6) | 3 (5.8) | 1 (1.3) | 5 (1.9)

Table 3 lists, by successful dose, adverse reactions with an overall frequency of ≥ 5% within the total population that occurred after a successful dose had been determined.

Table3: Adverse Reactions Which Occurred During Maintenance Therapy at a Frequency of ≥ 5%
System Organ Class Preferred term N (%) | 100 mcg (n=7) | 200 mcg (n=12) | 300 mcg (n=22) | 400 mcg (n=20) | 600 mcg (n=35) | 800 mcg (n=72) | Total (n=168)
Gastrointestinal disorders
Nausea | 1 (14.3) | 0 | 2 (9.1) | 0 | 1 (2.9) | 6 (8.3) | 10 (6.0)
Stomatitis | 0 | 1 (8.3) | 1 (4.5) | 0 | 0 | 1 (1.4) | 3 (1.8)
Constipation | 0 | 0 | 1 (4.5) | 2 (10.0) | 1 (2.9) | 4 (5.6) | 8 (4.8)
Dry mouth | 0 | 0 | 0 | 1 (5.0) | 2 (5.7) | 0 | 3 (1.8)
Nervous system disorders
Headache | 0 | 0 | 0 | 2 (10.0) | 1 (2.9) | 2 (2.8) | 5 (3.0)
Dysgeusia | 1 (14.3) | 0 | 0 | 0 | 0 | 1 (1.4) | 2 (1.2)
General disorders and administration site conditions
Fatigue | 0 | 0 | 0 | 1 (5.0) | 2 (5.7) | 0 | 3 (1.8)
Injury, poisoning and procedural complications
Accidental overdose | 1 (14.3) | 0 | 0 | 0 | 0 | 0 | 1 (0.6)
Respiratory, thoracic and mediastinal disorders
Dyspnoea | 0 | 1 (8.3) | 0 | 0 | 0 | 0 | 1 (0.6)
Skin and subcutaneous disorders
Hyperhidrosis | 1 (14.3) | 0 | 0 | 0 | 0 | 1 (1.4) | 2 (1.2)

The frequencies listed below represent adverse reactions that occurred in ≥ 1% of patients from two clinical trials who experienced that reaction while receiving ABSTRAL. Reactions are classified by system organ class.

Adverse Reactions (≥ 1%)

Cardiac disorders: bradycardia, tachycardia.

Eye disorders: vision blurred.

Gastrointestinal disorders: abdominal pain, abdominal pain upper, aphthous stomatitis, constipation, dry mouth, dyspepsia, gingival ulceration, impaired gastric emptying, lip ulceration, mouth ulceration, nausea, stomach discomfort, stomatitis, tongue disorder, vomiting.

General disorders and administration site conditions: asthenia, drug withdrawal syndrome, fatigue, malaise.

Immune system disorders: drug hypersensitivity.

Injury, poisoning and procedural complications: accidental overdose.

Metabolism and nutrition disorders: anorexia, decreased appetite.

Nervous system disorders: amnesia, disturbance in attention, dizziness, dysgeusia, headache, hypoesthesia, lethargy, parosmia, somnolence, tremor.

Psychiatric disorders: affect lability, anxiety, confusional state, depression, disorientation, dysphoria, euphoric mood, insomnia, mental status changes, paranoia, sleep disorder.

Reproductive system and breast disorders: erectile dysfunction.

Respiratory, thoracic and mediastinal disorder: dyspnea, oropharyngeal pain, throat tightness.

Skin and subcutaneous disorders: hyperhidrosis, night sweats, pruritus, rash, skin lesion.

Vascular disorders: hypotension.

7 DRUG INTERACTIONS

Fentanyl is metabolized mainly via the human cytochrome P450 3A4 isoenzyme system (CYP3A4); therefore potential interactions may occur when ABSTRAL is given concurrently with agents that affect CYP3A4 activity.

The concomitant use of ABSTRAL with CYP3A4 inhibitors (e.g., indinavir, nelfinavir, ritonavir, clarithromycin, itraconazole, ketoconazole, nefazodone, saquinavir, telithromycin, aprepitant, diltiazem, erythromycin, fluconazole, grapefruit juice, verapamil, or cimetidine) may result in a potentially dangerous increase in fentanyl plasma concentrations, which could increase or prolong adverse drug effects and may cause potentially fatal respiratory depression. Patients receiving ABSTRAL who begin therapy with, or increase the dose of, CYP3A4 inhibitors need to be carefully monitored for signs of opioid toxicity over an extended period of time. Increase dosage conservatively.

The concomitant use of ABSTRAL with CYP3A4 inducers (e.g., barbiturates, carbamazepine, efavirenz, glucocorticoids, modafinil, nevirapine, oxcarbazepine, phenobarbital, phenytoin, pioglitazone, rifabutin, rifampin, St. John's wort, or troglitazone) may result in a decrease in fentanyl plasma concentrations, which could decrease the efficacy of ABSTRAL.

Patients receiving ABSTRAL who stop therapy with, or decrease the dose of, CYP3A4 inducers need to be monitored for signs of increased ABSTRAL activity and the dose of ABSTRAL must be adjusted accordingly.

8 USE IN SPECIFIC POPULATIONS

8.1 Pregnancy - Category C

There are no adequate and well-controlled studies in pregnant women.

Use ABSTRAL during pregnancy only if the potential benefit justifies the potential risk to the fetus. No epidemiological studies of congenital anomalies in infants born to women treated with fentanyl during pregnancy have been reported.

Chronic maternal treatment with fentanyl during pregnancy has been associated with transient respiratory depression, behavioral changes, or seizures in newborn infants characteristic of neonatal abstinence syndrome.

In women treated acutely with intravenous or epidural fentanyl during labor, symptoms of neonatal respiratory or neurological depression were no more frequent than would be expected in infants of untreated mothers.

Transient neonatal muscular rigidity has been observed in infants whose mothers were treated with intravenous fentanyl.

Fentanyl is embryocidal in rats as evidenced by increased resorptions in pregnant rats at doses of 30 mcg/kg intravenously or 160 mcg/kg subcutaneously. Conversion to human equivalent doses indicates this is within the range of the human recommended dosing for ABSTRAL.

Fentanyl citrate was not teratogenic when administered to pregnant animals. Published studies demonstrated that administration of fentanyl (10, 100, or 500 mcg/kg/day) to pregnant rats from day 7 to 21, of their 21 day gestation, via implanted microosmotic minipumps, was not teratogenic (the high dose was approximately 6times the human dose of 800 mcg per pain episode on a mcg/m^2 basis). Intravenous administration of fentanyl (10 mcg/kg or 30 mcg/kg) to pregnant female rats from gestation day 6 to 18, was embryo- or feto-toxic, and caused a slightly increased mean delivery time in the 30 mcg/kg/day group, but was not teratogenic.

8.2 Labor and Delivery

Fentanyl readily crosses the placenta. Therefore do not use ABSTRAL during labor and delivery (including caesarean section) since it may cause respiratory depression in the fetus or in the newborn infant.

8.3 Nursing Mothers

Fentanyl is excreted in human milk; therefore, do not use ABSTRAL in women who are nursing because of the possibility of sedation and/or respiratory depression in their infants. Symptoms of opioid withdrawal may occur in infants at the cessation of nursing by women using ABSTRAL.

8.4 Pediatric Use

The safety and efficacy of ABSTRAL have not been established in patients below 18 years of age.

8.5 Geriatric Use

Of the 270 opioid tolerant patients with breakthrough cancer pain in the Phase 3 clinical studies of Abstral, 58 (21%) were 65 years of age and older. There was no difference in the median titrated dose in patients aged 65 years and older compared to those <65 years. No clinically meaningful difference was noted in the safety profile of the group 65 years of age and older as compared to younger patients in ABSTRAL clinical trials.

Elderly patients have been shown to be more sensitive to the effects of fentanyl when administered intravenously, compared with the younger adult population. Therefore, exercise caution when individually titrating ABSTRAL in elderly patients to provide adequate efficacy while minimizing risk.

8.6 Patients with Renal and Hepatic Impairment

Insufficient information exists to make recommendations regarding the use of ABSTRAL in patients with impaired renal or hepatic function. Fentanyl is metabolized primarily via human cytochrome P450 3A4 isoenzyme system and the inactive metabolite is mostly eliminated in urine. If the drug is used in these patients, use the drug with caution because of the reduced hepatic metabolism and renal excretion capacity in such patients.

8.7 Gender

Both male and female opioid-tolerant cancer patients were studied for the treatment of breakthrough cancer pain. No clinically relevant gender differences were noted either in efficacy or in observed adverse reactions.

9 DRUG ABUSE AND DEPENDENCE

9.1 Controlled Substance

ABSTRAL contains fentanyl, a Schedule II substance. Schedule II opioid substances such as fentanyl, hydromorphone, methadone, morphine, oxycodone, and oxymorphone have a high potential for abuse and addiction. ABSTRAL is also subject to misuse and criminal diversion.

9.2 Abuse and Addiction

Manage the handling of ABSTRAL to minimize the risk of misuse, including the restriction of access and accounting procedures as appropriate to the clinical setting and as required by law [see How Supplied/Storage and Handling (16.2, 16.3)].

Concerns about abuse, addiction, and diversion must not prevent the proper management of pain. However, all patients treated with opioids require careful monitoring for signs of abuse and addiction, because use of opioid analgesic products carries the risk of addiction even under appropriate medical use.

Addiction is a primary, chronic, neurobiologic disease, with genetic, psychosocial, and environmental factors influencing its development and manifestations. It is characterized by behaviors that include one or more of the following: impaired control over drug use, compulsive use, continued use despite harm, and craving. Drug addiction is a treatable disease, utilizing a multidisciplinary approach, but relapse is common. "Drug-seeking" behavior is very common in addicts and drug abusers.

Abuse and addiction are separate and distinct from physical dependence and tolerance. Be aware that addiction may not be accompanied by concurrent tolerance and symptoms of physical dependence in all addicts. In addition, abuse of opioids can occur in the absence of addiction and is characterized by misuse for non-medical purposes, often in combination with other psychoactive substances. Since ABSTRAL may be diverted for nonmedical use, careful record keeping of prescribing information, including quantity, frequency, and renewal requests is strongly advised.

Proper patient assessment, safe prescribing practices, periodic re-evaluation of therapy, and proper dispensing and storage are appropriate measures that help to limit abuse of opioid drugs.

Contact your State Professional Licensing Board, or State Controlled Substances Authority for information on how to prevent and detect abuse or diversion of this product.

9.3 Dependence

Physical dependence is not ordinarily a concern in the treatment of patients with chronic cancer pain, and fear of tolerance and physical dependence must not deter using opiate doses that adequately relieve the pain. Guide the administration of Abstral by the response of the patient.

Opioid analgesics may cause physical dependence that can result in withdrawal symptoms in patients who abruptly discontinue the drug. Withdrawal also may be precipitated through the administration of drugs with opioid antagonist activity (e.g., naloxone, nalmefene) or mixed agonist/antagonist analgesics (pentazocine, butorphanol, buprenorphine, nalbuphine).

Physical dependence usually does not occur to a clinically significant degree until after several weeks of continued opioid usage. Tolerance, in which increasingly larger doses are required in order to produce the same degree of analgesia, is initially manifested by a shortened duration of analgesic effect, and subsequently, by decreases in the intensity of analgesia.

10 OVERDOSAGE

10.1 Clinical Presentation

The manifestations of ABSTRAL overdosage are expected to be similar in nature to intravenous fentanyl and other opioids, and are an extension of its pharmacological actions with the most serious significant effect being hypoventilation [see Clinical Pharmacology (12.2)].

10.2 Immediate Management

Immediate management of opioid overdose includes removal of the ABSTRAL tablet, if still in the mouth, ensuring a patent airway, physical and verbal stimulation of the patient, and assessment of level of consciousness, ventilatory and circulatory status.

10.3 Treatment of Overdosage (Accidental Ingestion) in the Opioid NON-Tolerant Person

Provide ventilatory support, obtain intravenous access, and administer naloxone or other opioid antagonists as clinically indicated. The duration of respiratory depression following overdose may be longer than the effects of the opioid antagonist's action (e.g., the half-life of naloxone ranges from 30 to 81 minutes) and repeated administration may be necessary. Consult the package insert of the individual opioid antagonist for details.

10.4 Treatment of Overdosage in Opioid-Tolerant Patients

Provide ventilatory support and obtain intravenous access as clinically indicated. Judicious use of naloxone or another opioid antagonist may be warranted in some instances, but at the risk of precipitating an acute withdrawal syndrome.

10.5 General Considerations for Overdose

Management of severe ABSTRAL overdose includes: securing a patent airway, assisting or controlling ventilation and establishing intravenous access. In the presence of hypoventilation or apnea, assist or control ventilation, and administer oxygen as indicated.

Carefully observe and appropriately manage patients with overdose until their clinical condition is well controlled.

Although muscle rigidity interfering with respiration has not been seen following the use of ABSTRAL, this is possible with fentanyl and other opioids. If it occurs, manage it by using assisted or controlled ventilation, by an opioid antagonist, and as a final alternative, by a neuromuscular blocking agent.

11 DESCRIPTION

ABSTRAL (fentanyl) sublingual tablet is a solid formulation of fentanyl citrate, a potent opioid analgesic intended for oral sublingual administration. ABSTRAL is formulated as a white tablet available in six strengths, distinguishable by the shape of the tablet and by de-bossing on the tablet surface.

Active Ingredient: Fentanyl citrate, USP is N-(1-Phenethyl-4-piperidyl) propionanilide citrate (1:1). Fentanyl is a highly lipophilic compound (octanol-water partition coefficient at pH 7.4 is 816:1) that is freely soluble in organic solvents and sparingly soluble in water (1:40). The molecular weight of the free base is 336.5 (the citrate salt is 528.6). The pKa of the tertiary nitrogens are 7.3 and 8.4. The compound has the following structural formula:

All tablet strengths are expressed as the amount of fentanyl free base, e.g., the 100 mcg strength tablet contains 100 mcg of fentanyl free base.

Inactive Ingredients: Croscarmellose sodium, magnesium stearate, mannitol, and silicified microcrystalline cellulose.

12 CLINICAL PHARMACOLOGY

12.1 Mechanism of Action

Fentanyl is a pure opioid agonist whose principal therapeutic action is analgesia. Other members of the class known as opioid agonists include substances such as morphine, oxycodone, hydromorphone, codeine, and hydrocodone.

12.2 Pharmacodynamics

Pharmacological effects of opioid agonists include anxiolysis, euphoria, feelings of relaxation, respiratory depression, constipation, miosis, cough suppression, and analgesia. Like all pure opioid agonist analgesics, with increasing doses there is increasing analgesia, unlike with mixed agonist/antagonists or non-opioid analgesics, where there is a limit to the analgesic effect with increasing doses. With pure opioid agonist analgesics, there is no defined maximum dose; the ceiling to analgesic effectiveness is imposed only by side effects, the more serious of which may include somnolence and respiratory depression. Analgesia

In general, the effective concentration and the concentration at which toxicity occurs increase with increasing tolerance with any and all opioids. The rate of development of tolerance varies widely among individuals. As a result, individually titrate the dose of ABSTRAL to achieve the desired effect [see Dosage and Administration (2)].

Central Nervous System

The precise mechanism of the analgesic action is unknown although fentanyl is known to be a μ-opioid receptor agonist. Specific CNS opioid receptors for endogenous compounds with opioid-like activity have been identified throughout the brain and spinal cord and play a role in the analgesic effects of this drug.

Fentanyl produces respiratory depression by direct action on brain stem respiratory centers. The respiratory depression involves both a reduction in the responsiveness of the brain stem to increases in carbon dioxide and to electrical stimulation.

Fentanyl causes miosis even in total darkness. Pinpoint pupils are a sign of opioid overdose but are not pathognomonic (e.g., pontine lesions of hemorrhagic or ischemic origin may produce similar findings).

Gastrointestinal System

Fentanyl causes a reduction in motility associated with an increase in smooth muscle tone in the antrum of the stomach and in the duodenum. Digestion of food is delayed in the small intestine and propulsive contractions are decreased. Propulsive peristaltic waves in the colon are decreased, while tone may be increased to the point of spasm resulting in constipation. Other opioid induced-effects may include a reduction in gastric, biliary and pancreatic secretions, spasm of the sphincter of Oddi, and transient elevations in serum amylase.

Cardiovascular System

Fentanyl may produce release of histamine with or without associated peripheral vasodilation. Manifestations of histamine release and/or peripheral vasodilation may include pruritus, flushing, red eyes, sweating, and/or orthostatic hypotension.

Endocrine System

Opioid agonists have been shown to have a variety of effects on the secretion of hormones. Opioids inhibit the secretion of ACTH, cortisol, and luteinizing hormone (LH) in humans. They also stimulate prolactin secretion, growth hormone (GH) secretion, and pancreatic secretion of insulin and glucagon in humans and other species (e.g., rats and dogs). Thyroid stimulating hormone (TSH) has been shown to be both inhibited and stimulated by opioids.

Respiratory System

All opioid mu-receptor agonists, including fentanyl, produce dose-dependent respiratory depression. The risk of respiratory depression is less in patients receiving chronic opioid therapy who develop tolerance to these effects. Peak respiratory depressive effects may be seen as early as 15 to 30 minutes from the start of oral transmucosal fentanyl citrate administration and may persist for several hours.

Serious or fatal respiratory depression can occur even at recommended doses. Fentanyl depresses the cough reflex as a result of its CNS activity. Although not observed with oral transmucosal fentanyl products in clinical trials, fentanyl given rapidly by intravenous injection in large doses may cause rigidity in the muscles of respiration resulting in respiratory difficulties. Therefore, be aware of this potential complication [see Boxed Warning - Warnings: Importance Of Proper Patient Selection and Potential for Abuse, Contraindications (4), Warnings And Precautions (5.1), Adverse Reactions (6), and Overdosage (10)].

12.3 Pharmacokinetics

Absorption

Fentanyl is a highly lipophilic drug. Orally administered fentanyl undergoes pronounced hepatic and intestinal first pass effects. Absorption of fentanyl from ABSTRAL sublingual tablets is mainly through the oral mucosa.

The bioavailability of ABSTRAL sublingual tablets has been calculated to be 54%.

Dose proportionality across the 100 mcg to 800 mcg ABSTRAL dose range has been demonstrated (Table4). Mean plasma fentanyl levels following single doses of ABSTRAL are shown in Figure 1. The median time to maximum plasma concentration (Tmax) across these four doses of ABSTRAL varied from 30 to 60 minutes (range of 15 - 240 minutes).

Figure 1: Mean (+/- SD) Plasma Fentanyl Concentration versus Time after Administration of Single Doses of 100 mcg, 200 mcg, 400 mcg and 800 mcg ABSTRAL to Healthy Subjects

Pharmacokinetic parameters are presented in Table 4.

Table 4. Mean (CV%) Fentanyl Pharmacokinetic Parameters after Single-Dose Administration of 100, 200, 400 and 800 mcg Doses of ABSTRAL to Healthy Subjects (n=12 per Dose Level)
Parameter | Unit |  | Abstral dose
Parameter | Unit | 100 mcg | 200 mcg | 400 mcg | 800 mcg
Cmax | (ng/mL) | 0.187 (33) | 0.302 (31) | 0.765 (38) | 1.42 (33)
Tmaxa | (min) | 30 [19-120] | 52 [16-240] | 60 [30-120] | 30 [15-60]
AUC0-inf | (ng.h/mL) | 0.974 (34) | 1.92 (27) | 5.49 (35) | 8.95 (33)
T1/2 | (h) | 5.02 (51) | 6.67 (30) | 13.5 (37) | 10.1 (34)
a: median (range)

In another study, dose proportionality between 800 mcg and 1600 mcg in Cmax and AUC has also been demonstrated.

Pharmacokinetic studies have shown that multiple tablets are bioequivalent to single tablets of the equivalent dose.

Distribution

Fentanyl is highly lipophilic. Animal data showed that following absorption, fentanyl is rapidly distributed to the brain, heart, lungs, kidneys and spleen followed by a slower redistribution to muscles and fat. The plasma protein binding of fentanyl is 80-85%. The main binding protein is alpha-1-acid glycoprotein, but both albumin and lipoproteins contribute to some extent. The free fraction of fentanyl increases with acidosis. The mean volume of distribution at steady state (Vss) was 4 L/kg. Metabolism

Fentanyl is metabolized in the liver and in the intestinal mucosa to norfentanyl by cytochrome P450 3A4 isoform. Norfentanyl was not found to be pharmacologically active in animal studies [see Drug Interactions (7)].

Elimination

Fentanyl is more than 90% eliminated by biotransformation to N-dealkylated and hydroxylated inactive metabolites. Less than 7% of the dose is excreted unchanged in the urine, and only about 1% is excreted unchanged in the feces. The metabolites are mainly excreted in the urine, while fecal excretion is less important. The total plasma clearance of fentanyl was 0.5 L/hr/kg (range 0.3 - 0.7 L/ hr/kg).

13 NONCLINICAL TOXICOLOGY

13.1 Carcinogenesis, Mutagenesis, Impairment of Fertility

Long-term studies in animals have not been performed to evaluate the carcinogenic potential of fentanyl.

Fentanyl citrate was not mutagenic in the in vitro Ames reverse mutation assay in S. typhimurium or E. coli, or the mouse lymphoma mutagenesis assay, and was not clastogenic in the in vivo mouse micronucleus assay.

Fentanyl has been shown to impair fertility in rats at doses of 30 mcg/kg intravenously and 160 mcg/kg subcutaneously. Conversion to the human equivalent doses indicates that this is within the range of the human recommended dosing for ABSTRAL.

14 CLINICAL STUDIES

The efficacy of ABSTRAL was investigated in a clinical trial in opioid tolerant adult patients experiencing breakthrough cancer pain. Breakthrough cancer pain was defined as a transient flare of moderate-to-severe pain occurring in patients with cancer experiencing persistent cancer pain otherwise controlled with maintenance doses of opioid medications including at least 60 mg morphine/day, 50 mcg transdermal fentanyl/hour, or an equianalgesic dose of another opioid for 1 week or longer. All patients were on stable doses of either long-acting oral opioids or transdermal fentanyl for their persistent cancer pain.

A double-blind, placebo-controlled, crossover study was performed in patients with cancer to evaluate the effectiveness of ABSTRAL for the treatment of breakthrough cancer pain. Open-label titration identified a dose of ABSTRAL in which a patient obtained adequate analgesia with tolerable side effects, within the range of 100 mcg to 800 mcg. In the double-blind efficacy study, patients who identified a successful dose were randomized to a sequence of 10 treatments; seven with ABSTRAL and three with placebo.

Of the 131 patients who entered the titration phase of the study, 78 (60%) achieved a successful dose during the titration phase. Sixty- six patients entered the double-blind phase and 60 completed the study. The dose of ABSTRAL was determined by titration starting at 100 mcg. The final titrated dose of ABSTRAL for breakthrough cancer pain was not predicted from the daily maintenance dose of opioid used to manage the persistent cancer pain. In a second open-label safety study using an identical titration regimen, 96 of 139 patients (69%) who entered the study titrated to a dose in which the patient obtained adequate analgesia with tolerable side effects during the titration phase. Table 5 presents the final titrated dose for both the doubleblind efficacy and open-label safety studies.

Table 5: Final dose of ABSTRAL following initial titration in all clinical efficacy and safety studies
ABSTRAL Dose | N=174 n (%)
100 mcg | 11 (6)
200 mcg | 15 (9)
300 mcg | 35 (20)
400 mcg | 25 (14)
600 mcg | 40 (23)
800 mcg | 48 (28)

The primary outcome measure, the mean sum of pain intensity difference at 30 minutes (SPID30) for ABSTRAL-treated episodes was statistically significantly higher than for placebo-treated episodes.

Figure 2: Mean Pain Intensity Difference (±SE) for ABSTRAL Compared to Placebo

16 HOW SUPPLIED/STORAGE AND HANDLING

16.1 Storage and Handling

ABSTRAL is supplied in individually sealed child-resistant blister packages contained in a cardboard outer carton, in pack sizes of 12 (100 mcg, 200 mcg, 300 mcg and 400 mcg strengths) or 32 (all strengths) tablets. The packaging is color-coded for each ABSTRAL tablet strength.

The amount of fentanyl contained in ABSTRAL can be fatal to a child, individual for whom it is not prescribed or non-opioid tolerant adult. Patients and their caregivers must be instructed to keep ABSTRAL out of the reach of children [see Boxed Warning - Warnings: Potential For Abuse and Importance Of Proper Patient Selection and Warnings And Precautions (5), and Patient Counseling Information (17.1)].

Store at 20-25°C (68-77°F); excursions permitted between 15-30°C (59-86°F) [see USP Controlled Room Temperature]. Protect from moisture.

16.2 Disposal of ABSTRAL

Patients and their household members must be advised to dispose of any tablets remaining from a prescription as soon as they are no longer needed. Instructions are included in Patient Counseling Information (17.2) and in the Medication Guide.

To dispose of any unused ABSTRAL tablets, remove them from the blister cards and flush down the toilet. Do not dispose of the ABSTRAL blister cards or cartons down the toilet.

If additional assistance is required, call Galena Biopharma, Inc. at 1-888-227-8725.

16.3 How Supplied

ABSTRAL is supplied in six dosage strengths. Tablets are supplied in child-resistant, protective blister cards with peelable foil. Each blister card contains 4 tablets, in pack sizes of 12 (100 mcg, 200 mcg, 300 mcg and 400 mcg strengths) or 32 (all strengths) tablets. Each tablet is white in color, with the strength distinguishable by the shape of the dosage unit and by de-bossing on the tablet surface:

Dosage Strength (fentanyl base) | Tablet Shape | Tablet Markings | Carton/Blister Package Color | Pack size | NDC Number
100 mcg | Round | "1" | Light blue | 12 | 57881-331-12
 |  |  |  | 32 | 57881-331-32
200 mcg | Oval | "2" | Dark orange | 12 | 57881-332-12
 |  |  |  | 32 | 57881-332-32
300 mcg | Triangle | "3" | Brown | 12 | 57881-333-12
 |  |  |  | 32 | 57881-333-32
400 mcg | Diamond | "4" | Violet | 12 | 57881-334-12
 |  |  |  | 32 | 57881-334-32
600 mcg | "D" | "6" | Turquoise | 32 | 57881-336-32
800 mcg | Capsule | "8" | Indigo | 32 | 57881-338-32

Note: Colors and shapes are a secondary aid in product identification. Please be sure to confirm the printed dosage before dispensing.

17 PATIENT COUNSELING INFORMATION

See FDA-approved patient labeling (Medication Guide)

Patient/Caregiver Instructions

- Before initiating treatment with Abstral, explain the statements below to patients and/or caregivers. Instruct patients to read the Medication Guide each time Abstral is dispensed because new information may be available.
- TIRF REMS Access Program
  - Outpatients must be enrolled in the TIRF REMS Access program before they can receive Abstral.
  - Allow patients the opportunity to ask questions and discuss any concerns regarding Abstral or the TIRF REMS Access program.
  - As a component of the TIRF REMS Access program, prescribers must review the contents of the Abstral Medication Guide with every patient before initiating treatment with Abstral.
  - Advise the patient that Abstral is available only from pharmacies that are enrolled in the TIRF REMS Access program, and provide them with the telephone number and website for information on how to obtain the drug.
  - Advise the outpatient that only enrolled health care providers may prescribe Abstral.
  - Patient must sign the Patient-Prescriber Agreement to acknowledge that they understand the risks of Abstral.
  - Advise patients that they may be requested to participate in a survey to evaluate the effectiveness of the TIRF REMS Access program.
- Instruct patients and their caregivers that ABSTRAL contains medicine in an amount that could be fatal in children, in individuals for whom ABSTRAL is not prescribed, and in those who are not opioid tolerant.
  Patients and their caregivers must be instructed to keep ABSTRAL, both used and unused dosage units, out of the reach of children. Patients and their caregivers must be instructed to dispose of any unneeded tablets remaining from a prescription as soon as possible [see How Supplied/Storage and Handling (16.2), and Warnings and Precautions (5.2).]
- Instruct patients and their caregivers to read the Medication Guide each time ABSTRAL is dispensed because new information may be available.
- Instruct patients not to take Abstral for acute pain, postoperative pain, pain from injuries, headache, migraine, or any other short- term pain, even if they have taken other opioid analgesics for these conditions.
- Instruct patients on the meaning of opioid tolerance and Abstral is only to be used as a supplemental pain medication for patients with pain requiring regular opioids, who have developed tolerance to the opioid medication and who need additional opioid treatment of breakthrough pain episodes.
- Instruct that if they are not taking an opioid medication on a regular around-the-clock basis, they must not take Abstral.
- You must not take more than 2 doses of ABSTRAL for each episode of breakthrough cancer pain.
- You must wait two hours before treating a new episode of breakthrough pain with ABSTRAL.
- Instruct patients NOT to share Abstral and that sharing Abstral with anyone else could result in the other individual's death due to overdose.
- Advise patients that Abstral contains fentanyl, which is a pain medication similar to hydromorphone, methadone, morphine, oxycodone, and oxymorphone.
- Advise patients that the active ingredient in Abstral, fentanyl, is a drug that some people abuse. Abstral is to be taken only by the patient for whom it was prescribed, and protected from theft or misuse in the work or home environments.
- Instruct patients to talk to their doctor if breakthrough pain is not alleviated or worsens after taking Abstral.
- Instruct patients to use Abstral exactly as prescribed by their doctor and not to take Abstral more often than prescribed.
- Caution patients that Abstral can affect a person's ability to perform activities that require a high level of attention (such as driving or using heavy machinery). Warn patients taking Abstral of these dangers and counsel accordingly.
- Warn patients not to combine Abstral with alcohol, sleep aids, or tranquilizers except by order of the prescribing physician, because dangerous additive effects may occur resulting in serious injury or death.
- Inform female patients that if they become pregnant or plan to become pregnant during treatment with Abstral to ask their doctor about the effects that Abstral (or any medicine) may have on them and their unborn child.

Disposal of Unopened ABSTRAL Blister Packages When No Longer Needed

- Advise patients and their household members to dispose of any unopened packs remaining from a prescription as soon as they are no longer needed.
- Instruct patients that, to dispose of any unused ABSTRAL tablets, remove them from the blister cards and flush them down the toilet. Do not dispose of the ABSTRAL blister cards or cartons down the toilet.
- Detailed instructions for the proper storage, administration, disposal, and important instructions for managing an overdose of ABSTRAL are provided in the ABSTRAL Medication Guide. Ensure patients read this information in its entirety and give them an opportunity to have their questions answered.
- In the event that a caregiver requires additional assistance in disposing of excess units that remain in the home after the drug is no longer needed, instruct them to call the toll-free number for Galena Biopharma, Inc. 1-888-227-8725 or seek assistance from their local DEA office.

Medication Guide
ABSTRAL® (AB-stral) CII
(fentanyl)
Sublingual tablets

100 mcg, 200 mcg, 300 mcg, 400 mcg, 600 mcg, 800 mcg

IMPORTANT:
Do not use ABSTRAL unless you are regularly using another opioid pain medicine around-the-clock for your cancer pain and your body is used to these medicines (this means that you are opioid tolerant).
Keep ABSTRAL in a safe place away from children.
Get emergency medical help right away if:

- a child takes ABSTRAL. ABSTRAL can cause an overdose and death in any child who takes it.
- an adult who has not been prescribed ABSTRAL takes it
- an adult who is not already taking opioids around-the-clock, takes ABSTRAL

These are medical emergencies that can cause death. If possible, try to remove ABSTRAL from the mouth.

Read this Medication Guide completely before you start taking ABSTRAL, and each time you get a new prescription. There may be new information. This Medication Guide does not take the place of talking to your healthcare provider about your medical condition or your treatment. Be sure to share this important information with members of your household and other caregivers.

What is the most important information I should know about ABSTRAL?

ABSTRAL can cause life-threatening breathing problems which can lead to death.

1. Do not take ABSTRAL if you are not opioid tolerant.
2. If you stop taking your around-the-clock opioid pain medicine for your cancer pain, you must stop taking ABSTRAL. You may no longer be opioid tolerant. Talk to your healthcare provider about how to treat your pain.
3. Take ABSTRAL exactly as prescribed by your healthcare provider.
  - You must not take more than 2 doses of ABSTRAL for each episode of breakthrough cancer pain.
  - You must wait two hours before treating a new episode of breakthrough pain with ABSTRAL. See the Medication Guide section "How should I take ABSTRAL?" and the Patient Instructions for Use at the end of this Medication Guide for detailed information about how to take ABSTRAL the right way.
4. Do not switch from ABSTRAL to other medicines that contain fentanyl without talking with your healthcare provider. The amount of fentanyl in a dose of ABSTRAL is not the same as the amount of fentanyl in other medicines that contain fentanyl. Your healthcare provider will prescribe a starting dose of ABSTRAL that may be different than other fentanyl containing medicines you may have been taking.
5. Do not take ABSTRAL for short-term pain that you would expect to go away in a few days, such as:
  - pain after surgery
  - headache or migraine
  - dental pain
6. Never give ABSTRAL to anyone else, even if they have the same symptoms you have. It may harm them or even cause death.
  ABSTRAL is a federally controlled substance (CII) because it is a strong opioid (narcotic) pain medicine that can be misused by people who abuse prescription medicines or street drugs.
  - Prevent theft, misuse or abuse. Keep ABSTRAL in a safe place to protect it from being stolen.
    ABSTRAL can be a target for people who abuse opioid (narcotic) medicines or street drugs.
  - Selling or giving away this medicine is against the law.
7. ABSTRAL is available only through a program called the TIRF (Transmucosal Immediate-Release Fentanyl) REMS (Risk Evaluation and Mitigation Strategy) Access program. To receive ABSTRAL, you must:
  - talk to your healthcare provider
  - understand the benefits and risks of ABSTRAL
  - agree to all of the instructions
  - sign the Patient-Prescriber Agreement form

What is ABSTRAL?

- ABSTRAL is a prescription medicine that contains the medicine fentanyl.
- ABSTRAL is used to manage breakthrough pain in adults with cancer (18 years of age and older) who are already routinely taking other opioid pain medicines around-the-clock for cancer pain.
- ABSTRAL is started only after you have been taking other opioid pain medicines and your body has become used to them (you are opioid tolerant). Do not use ABSTRAL if you are not opioid tolerant.
- ABSTRAL is a small tablet that is placed on the floor of the mouth under your tongue (sublingual) and allowed to dissolve.
- You must stay under your healthcare provider's care while taking ABSTRAL.
- ABSTRAL is only:
  - available through the TIRF REMS Access program
  - given to people who are opioid tolerant

It is not known if ABSTRAL is safe and effective in children under 18 years of age.

Who should not take ABSTRAL?

Do not take ABSTRAL:

- if you are not opioid tolerant. Opioid tolerant means that you are already taking other opioid pain medicines around-the- clock for your cancer pain, and your body is used to these medicines.
- for short-term pain that you would expect to go away in a few days, such as:
  - pain after surgery
  - headache or migraine
  - dental pain
- if you are allergic to any of the ingredients in ABSTRAL. See the end of this Medication Guide for a complete list of other ingredients in ABSTRAL.

What should I tell my healthcare provider before taking ABSTRAL?

Before taking ABSTRAL, tell your healthcare provider if you:

- have trouble breathing or lung problems such as asthma, wheezing, or shortness of breath
- have or had a head injury or brain problem
- have liver or kidney problems
- have seizures
- have a slow heart rate or other heart problems
- have low blood pressure
- have mental health problems including major depression, schizophrenia or hallucinations (seeing or hearing things that are not there)
- have a past or present drinking problem (alcoholism), or a family history of drinking problems
- have a past or present drug abuse problem or addiction problem, or a family history of a drug abuse problem or addiction problem
- have any other medical conditions
- are pregnant or plan to become pregnant. ABSTRAL may cause serious harm to your unborn baby.
- are breastfeeding or plan to breastfeed. ABSTRAL can pass into your breast milk. It can cause serious harm to your baby. You should not use ABSTRAL while breastfeeding.

Tell your healthcare provider about all the medicines you take, including prescription and non-prescription medicines, vitamins, and herbal supplements. Some medicines may cause serious or life-threatening side effects when taken with ABSTRAL. Sometimes, the doses of certain medicines and ABSTRAL may need to be changed if used together.

- Do not take any medicine while using ABSTRAL until you have talked to your healthcare provider. Your healthcare provider will tell you if it is safe to take other medicines while you are using ABSTRAL.
- Be very careful about taking other medicines that may make you sleepy, such as other pain medicines, anti-depressants, sleeping pills, anti-anxiety medicines, antihistamines, or tranquilizers.

Know the medicines you take. Keep a list of them to show your healthcare provider and pharmacist when you get a new medicine.

How should I take ABSTRAL?

Before you can begin to take ABSTRAL:

- Your healthcare provider will explain the TIRF REMS Access program to you.
- You will sign the TIRF REMS Access program Patient-Prescriber Agreement form.
- ABSTRAL is only available at pharmacies that are part of the TIRF REMS Access program. Your healthcare provider will let you know the pharmacy closest to your home where you can have your ABSTRAL prescription filled.

Taking ABSTRAL:

- Take ABSTRAL exactly as prescribed. Do not take ABSTRAL more often than prescribed.
- If you notice that your tablets are a different shape or color, be sure to check with your pharmacist to make sure you have the right strength of medicine.
- Do not suck, chew or swallow the tablet.
- See the detailed Patient Instructions for Use at the end of this Medication Guide for information about how to take ABSTRAL the right way.
- Your healthcare provider will change the dose until you and your healthcare provider find the right dose for you.
- You must not use more than 2 doses of ABSTRAL for each episode of breakthrough cancer pain:
  - Take 1 dose for an episode of breakthrough cancer pain. o If your breakthrough pain does not get better within 30 minutes after taking the first dose of
  - ABSTRAL, you can take 1 more dose of ABSTRAL as instructed by your healthcare provider.
  - If your breakthrough pain does not get better after the second dose of ABSTRAL, call your healthcare provider for instructions. Do not take another dose of ABSTRAL at this time.
- Wait at least 2 hours before treating a new episode of breakthrough cancer pain with ABSTRAL:
  - If you only need to take 1 dose of ABSTRAL for an episode of breakthrough pain, you must wait 2 hours from the time of that dose to take a dose of ABSTRAL for a new episode of breakthrough pain
  - If you need to take 2 doses of ABSTRAL for an episode of breakthrough pain, you must wait 2 hours after the second dose to take a dose of ABSTRAL for a new episode of breakthrough pain.
- It is important for you to keep taking your around-the-clock opioid pain medicine while taking ABSTRAL.
- Talk to your healthcare provider if your dose of ABSTRAL does not relieve your breakthrough cancer pain. Your healthcare provider will decide if your dose of ABSTRAL needs to be changed.
- Talk to your healthcare provider if you have more than 4 episodes of breakthrough cancer pain per day. The dose of your around- the-clock opioid pain medicine may need to be adjusted.
- If you take too much ABSTRAL or overdose, you or your caregiver should call for emergency medical help or have someone take you to the nearest hospital emergency room right away.

What should I avoid while taking ABSTRAL?

- Do not drive, operate heavy machinery, or do other dangerous activities until you know how ABSTRAL affects you. ABSTRAL can make you sleepy. Ask your healthcare provider when it is okay to do these activities.
- Do not drink alcohol while using ABSTRAL. It can increase your chance of getting dangerous side effects.

What are the possible side effects of ABSTRAL?

ABSTRAL can cause serious side effects, including:

1. Breathing problems that can become life-threatening. See "What is the most important information I should know about ABSTRAL?"
  - Call your healthcare provider or get emergency medical help right away if you:
    - have trouble breathing
    - have drowsiness with slowed breathing
    - have shallow breathing (little chest movement with breathing)
    - feel faint, very dizzy, confused, or have other unusual symptoms
    These symptoms can be a sign that you have taken too much ABSTRAL or the dose is too high for you. These symptoms may lead to serious problems or death if not treated right away. If you have any of these symptoms, do not take any more ABSTRAL until you have talked to your healthcare provider.
2. Decreased blood pressure. This can make you feel dizzy or lightheaded if you get up too fast from sitting or lying down.
3. Physical dependence. Do not stop taking ABSTRAL or any other opioid, without talking to your healthcare provider. You could become sick with uncomfortable withdrawal symptoms because your body has become used to these medicines. Physical dependency is not the same as drug addiction.
4. A chance of abuse or addiction. This chance is higher if you are or have ever been addicted to or abused other medicines, street drugs, or alcohol, or if you have a history of mental health problems.

The most common side effects of ABSTRAL are:

- nausea
- sleepiness
- headache

Constipation (not often enough or hard bowel movements) is a very common side effect of pain medicines (opioids) including ABSTRAL and is unlikely to go away without treatment. Talk to your healthcare provider about dietary changes, and the use of laxatives (medicines to treat constipation) and stool softeners to prevent or treat constipation while taking ABSTRAL.

Tell your healthcare provider if you have any side effect that bothers you or that does not go away.

These are not all the possible side effects of ABSTRAL. For more information, ask your healthcare provider or pharmacist.

Call your doctor for medical advice about your side effects. You may report side effects to FDA at 1-800FDA-1088.

How should I store ABSTRAL?

- Always keep ABSTRAL in a safe place away from children and from anyone for whom it has not been prescribed. Protect ABSTRAL from theft.
- Store ABSTRAL at room temperature, 59°F to 86°F (15°C to 30°C) until ready to use.
- Keep ABSTRAL in the original blister unit. Do not remove ABSTRAL tablets from their blister packaging for storage in a temporary container, such as a pillbox.

How should I dispose of unopened ABSTRAL tablets when they are no longer needed?

- Dispose of any unopened ABSTRAL units remaining from a prescription as soon as you no longer need them:
  - remove the tablets from the blister cards and flush them down the toilet.
- Do not flush the ABSTRAL blister cards, units or cartons down the toilet.
- If you need help with disposal of ABSTRAL, call Galena Biopharma, Inc.., at 1-888-227-8725 or call your local Drug Enforcement Agency (DEA) office.

General information about ABSTRAL

Medicines are sometimes prescribed for purposes other than those listed in a Medication Guide. Use ABSTRAL only for the purpose for which it was prescribed. Do not give ABSTRAL to other people, even if they have the same symptoms you have. ABSTRAL can harm other people and even cause death. Sharing ABSTRAL is against the law.

This Medication Guide summarizes the most important information about ABSTRAL. If you would like more information, talk with your healthcare provider or pharmacist. You can ask your pharmacist or healthcare provider for information about ABSTRAL that is written for healthcare professionals.

For more information about the TIRF REMS Access program, go to www.TIRFREMSAccess.com or call 1866-822-1483.

What are the ingredients in ABSTRAL?

Active Ingredient: fentanyl citrate

Inactive Ingredients: croscarmellose sodium, magnesium stearate, mannitol, and silicified microcrystalline cellulose.

Patient Instructions for Use

Before you take ABSTRAL, it is important that you read the Medication Guide and these Patient Instructions for Use. Be sure that you read, understand, and follow these Patient Instructions for Use so that you take ABSTRAL the right way. Ask your healthcare provider or pharmacist if you have questions about the right way to take ABSTRAL.

When you get an episode of breakthrough pain, take the dose prescribed by your healthcare provider as follows:

- If your mouth is dry, take a sip of water to moisten it. Spit out or swallow the water. Dry your hands if they are wet before you handle ABSTRAL tablets.
- ABSTRAL comes in a blister card with 4 blister units. Each blister unit contains an ABSTRAL tablet. It is important that the tablet stays sealed in the blister unit until you are ready to use it.
- When you are ready to take an ABSTRAL tablet, pull apart 1 of the blister units from the blister card by tearing along the dotted lines (perforations) until it is fully separated. (See Figures 1 and 2)
- When the blister unit is fully separated, peel back the foil starting at the unsealed area where indicated. Gently remove the tablet. Do not try to push ABSTRAL tablets through the foil. This will damage the tablet. (See Figures 3 and 4)
- As soon as you remove the ABSTRAL tablet from the blister unit:
  - place it on the floor of your mouth, under your tongue, as far back as you can (See Figures 5, 6, and 7).
  - If more than 1 tablet is required, spread them around the floor of your mouth under your tongue.
  - Let the tablet dissolve completely.
  - ABSTRAL dissolves under your tongue and will be absorbed by your body to help provide relief for your breakthrough cancer pain.
  - Do not suck, chew or swallow the tablet.
  - You should not drink or eat anything until the tablet has completely dissolved under your tongue and you can no longer feel it in your mouth.

Manufactured by:
Pharmaceutics International, Inc.
Hunt Valley, MD 21031

Manufactured for:
Galena Biopharma, Inc.
Portland, OR 97239

Issued: November 2014

This Medication Guide has been approved by the U.S. Food and Drug Administration. Copyright © 2013, Galena Biopharma, Inc. All rights reserved.

ABSTRAL and Galena Biopharma are trademarks owned by the Galena Biopharma, Inc.

Principal Display Panel – 100 mcg Carton Label

ABSTRAL® CII

(fentanyl) sublingual tablets

NDC 57881-331-32

Rx only

equivalent to 100 mcg fentanyl base

32 Sublingual Tablets

(4 tablets x 8 cards)

Mfd. by: Pharmaceutics International, Inc., Hunt Valley, MD 21031

Mfd. for: Galena Biopharma Inc., Suite 208, 310 N. State St., Lake Oswego, OR 97034

For questions about ABSTRAL® call: 1-888-ABSTRAL.

Principal Display Panel – 200 mcg Carton Label

ABSTRAL® CII

(fentanyl) sublingual tablets

NDC 57881-332-32

Rx only

equivalent to 200 mcg fentanyl base

32 Sublingual Tablets

(4 tablets x 8 cards)

Mfd. by: Pharmaceutics International, Inc., Hunt Valley, MD 21031

Mfd. for: Galena Biopharma Inc., Suite 208, 310 N. State St., Lake Oswego, OR 97034

For questions about ABSTRAL® call: 1-888-ABSTRAL.

Principal Display Panel – 300 mcg Carton Label

ABSTRAL® CII

(fentanyl) sublingual tablets

NDC 57881-333-32

Rx only

equivalent to 300 mcg fentanyl base

32 Sublingual Tablets

(4 tablets x 8 cards)

Mfd. by: Pharmaceutics International, Inc., Hunt Valley, MD 21031

Mfd. for: Galena Biopharma Inc., Suite 208, 310 N. State St., Lake Oswego, OR 97034

For questions about ABSTRAL® call: 1-888-ABSTRAL.

Principal Display Panel – 400 mcg Carton Label

ABSTRAL® CII

(fentanyl) sublingual tablets

NDC 57881-334-32

Rx only

equivalent to 400 mcg fentanyl base

32 Sublingual Tablets

(4 tablets x 8 cards)

Mfd. by: Pharmaceutics International, Inc., Hunt Valley, MD 21031

Mfd. for: Galena Biopharma Inc., Suite 208, 310 N. State St., Lake Oswego, OR 97034

For questions about ABSTRAL® call: 1-888-ABSTRAL.

Principal Display Panel – 600 mcg Carton Label

ABSTRAL® CII

(fentanyl) sublingual tablets

NDC 57881-336-32

Rx only

equivalent to 600 mcg fentanyl base

32 Sublingual Tablets

(4 tablets x 8 cards)

Mfd. by: Pharmaceutics International, Inc., Hunt Valley, MD 21031

Mfd. for: Galena Biopharma Inc., Suite 208, 310 N. State St., Lake Oswego, OR 97034

For questions about ABSTRAL® call: 1-888-ABSTRAL.

Principal Display Panel – 800 mcg Carton Label

ABSTRAL® CII

(fentanyl) sublingual tablets

NDC 57881-338-32

Rx only

equivalent to 800 mcg fentanyl base

32 Sublingual Tablets

(4 tablets x 8 cards)

Mfd. by: Pharmaceutics International, Inc., Hunt Valley, MD 21031

Mfd. for: Galena Biopharma Inc., Suite 208, 310 N. State St., Lake Oswego, OR 97034

For questions about ABSTRAL® call: 1-888-ABSTRAL.